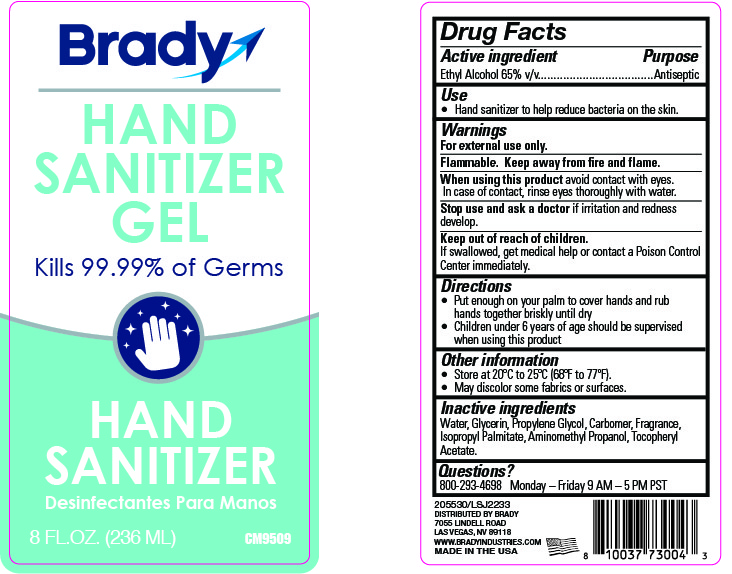 DRUG LABEL: Hand Sanitizer
NDC: 79258-100 | Form: GEL
Manufacturer: Brady Industries, Inc.
Category: otc | Type: HUMAN OTC DRUG LABEL
Date: 20200623

ACTIVE INGREDIENTS: ALCOHOL 65 mL/100 mL
INACTIVE INGREDIENTS: AMINOMETHYLPROPANOL; GLYCERIN; CARBOMER 940; ISOPROPYL PALMITATE; WATER; .ALPHA.-TOCOPHEROL ACETATE

Drug Facts

Active Ingredient(s)

Ethyl Alcohol 65% v/v. Purpose: Antiseptic

Purpose

Antiseptic, Hand Sanitizer

Use

Hand Sanitizer to help reduce bacteria on the skin.

Warnings

For external use only. Flammable.

Do not use

- in children less than 2 months of age
- on open skin wounds

When using this product keep out of eyes, ears, and mouth. In case of contact with eyes, rinse eyes thoroughly with water.
Stop use and ask a doctor if irritation or rash occurs. These may be signs of a serious condition.
Keep out of reach of children. If swallowed, get medical help or contact a Poison Control Center right away.

Stop use and ask a doctor if irritation or rash occurs.

Keep out of reach of children. If swallowed, get medical help or contact a Poison Control Center right away.

Directions

- Place enough product to cover hands and rub hands together briskly until dry.
- Supervise children under 6 years of age when using this product.

Other information

- Store between 20-25C (68-77F)
- May discolor some fabrics or surfaces

Inactive ingredients

Water, Glycerin, Propylene Glycol, Carbomer, Fragrance, Isopropyl Palmitate, Aminomethyl Propanol,Tocopheryl Acetate.

Package Label - Principal Display Panel

NDC:79258-100-08 8oz Hand Sanitizer Gel